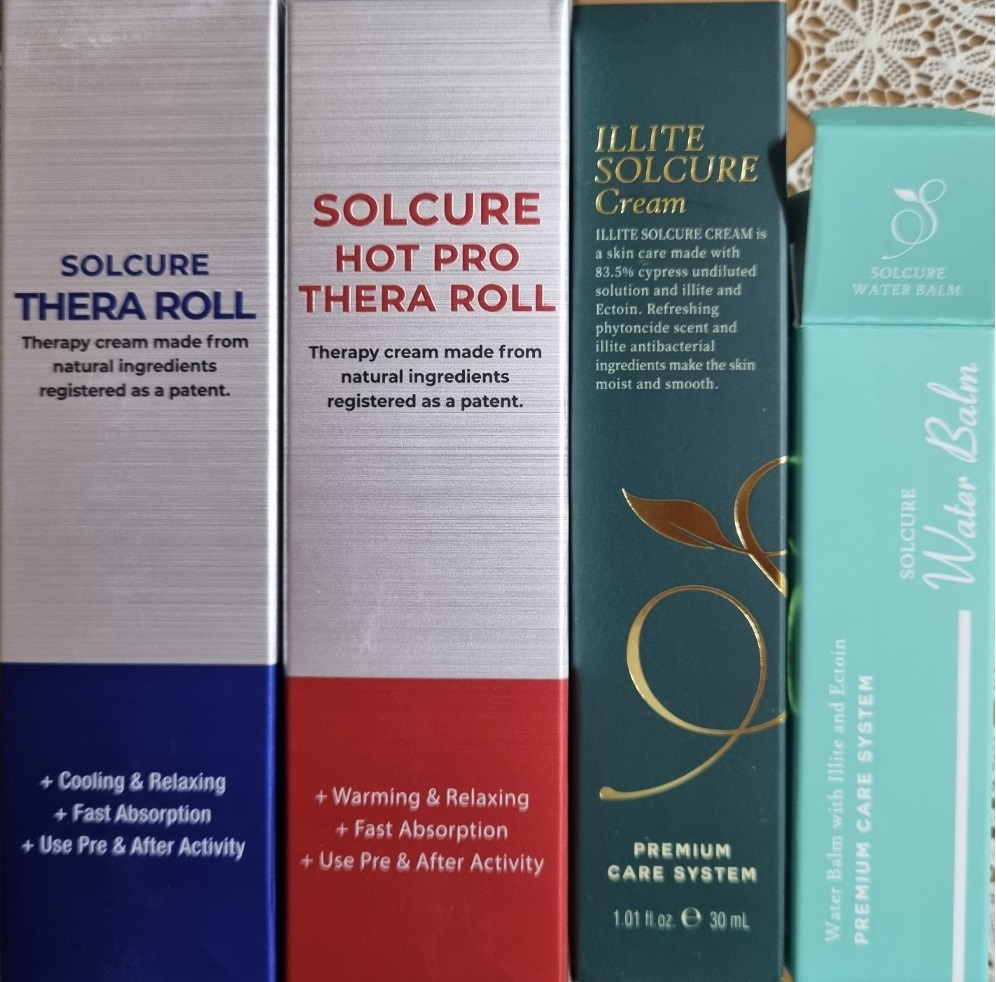 DRUG LABEL: Solcure Water Balm
NDC: 83235-0003 | Form: STICK
Manufacturer: Erae Natural Life
Category: otc | Type: HUMAN OTC DRUG LABEL
Date: 20230201

ACTIVE INGREDIENTS: LEDIKITE 0.01 g/100 g
INACTIVE INGREDIENTS: WATER; GLYCERIN

Drug Facts

ACTIVE INGREDIENT

illite

INACTIVE INGREDIENT

Glycerin
Dipropylene Glycol
Chamaecyparis Obtusa Water
Water
Palmitic acid
Stearic Acid
Ectoin
Vincetoxicum Atratum Extract
Butylene Glycol
Fucus Vesiculosus Extract
Prunella Vulgaris Extract
Sodium Hydroxide

PURPOSE

skin protentant

keep out or reach of the children

INDICATIONS AND USAGE

Apply an appropriate amount to the skin

WARNINGS

This product is for exeternal use only. Do not use for internal use
Storage and handling precautions
If possible, avoid direct sunlight and store in cool and area of low humidity in order to maintain the quality of the product and avoid misuse
Avoid placing the product near fire and store out in reach of children

- consult a physician in case of abnormal symptoms, such as red spots, swelling or itching, or side effects in the areas of application due to direct light during or after using the product

- do not use on wounded area

DOSAGE AND ADMINISTRATION

for external use only